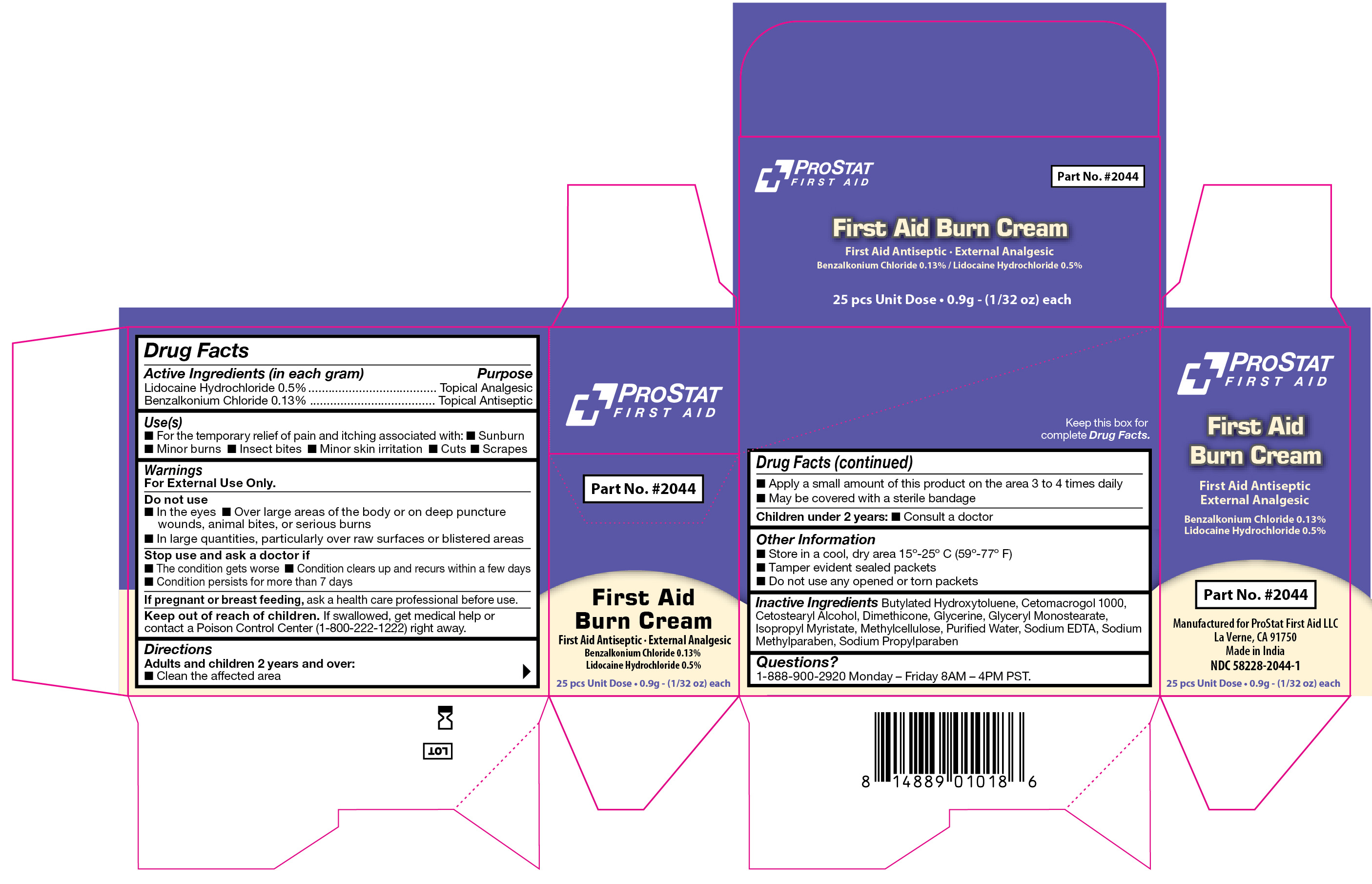 DRUG LABEL: First Aid Burn Cream
NDC: 58228-2044 | Form: CREAM
Manufacturer: ProStat First Aid LLC
Category: otc | Type: HUMAN OTC DRUG LABEL
Date: 20251215

ACTIVE INGREDIENTS: LIDOCAINE HYDROCHLORIDE 0.5 g/100 g; BENZALKONIUM CHLORIDE 0.13 g/100 g
INACTIVE INGREDIENTS: BUTYLATED HYDROXYTOLUENE; CETOSTEARYL ALCOHOL; GLYCERIN; GLYCERYL MONOSTEARATE; ISOPROPYL MYRISTATE; METHYLPARABEN SODIUM; PROPYLPARABEN SODIUM; METHYLCELLULOSE (4000 CPS); WATER; EDETATE SODIUM; CETETH-20; DIMETHICONE 350

2044 First Aid Burn Cream

Active Ingredient

Benzalkonium Chloride 0.13%

Active Ingredient

Lidocaine Hydrochloride 0.5%

Purpose

Benzalkonium Chloride Topical Antiseptic

Lidocaine Hydrochloride Topical Analgesic

Use(s)

• For the temporary relief of pain and itching associated with:

• Sunburn • Minor burns • Insect bites • Minor skin irritation • Cuts • Scrapes

Warnings

For External Use Only

Do not use

• In the eyes

• Over large areas of the body or on deep puncture wounds, animal bites, or serious burns

• In large quantities, particularly over raw surfaces or blistered areas

Stop use and ask a dioctor if

• The condition gets worse

• Condition clears up and recurs within a few days

• Condition persists for more than 7 days

If pregnant or breast feeding

ask a health care professional before use.

Keep out of reach of children

If swallowed, get medical help or contact a Poison Control Center (1-800-222-1222) right away.

Directions

Adults and children 2 years and over:

• Clean the affected area

• Apply a small amount of this product on the area 3 to 4 times daily

• May be covered with a sterile bandage

Children under 2 years:

• Consult a doctor

Other Information

• Store in a cool, dry area 15º-25ºC (59º-77ºF)

• Tamper evident sealed packets

• Do not use any opened or torn packets

Inactive Ingredients

Butylated Hydroxytoluene, Cetomacrogol 1000, Cetostearyl Alcohol, Dimethicone, Glycerine, Glyceryl Monostearate, Isopropyl Myristate, Methylcellulose, Purified Water, Sodium EDTA, Sodium Methylparaben, Sodium Propylparaben

Questions?

1-888-900-2920 Monday - Friday 8AM - 4PM PST.

Label

First Aid Burn Cream